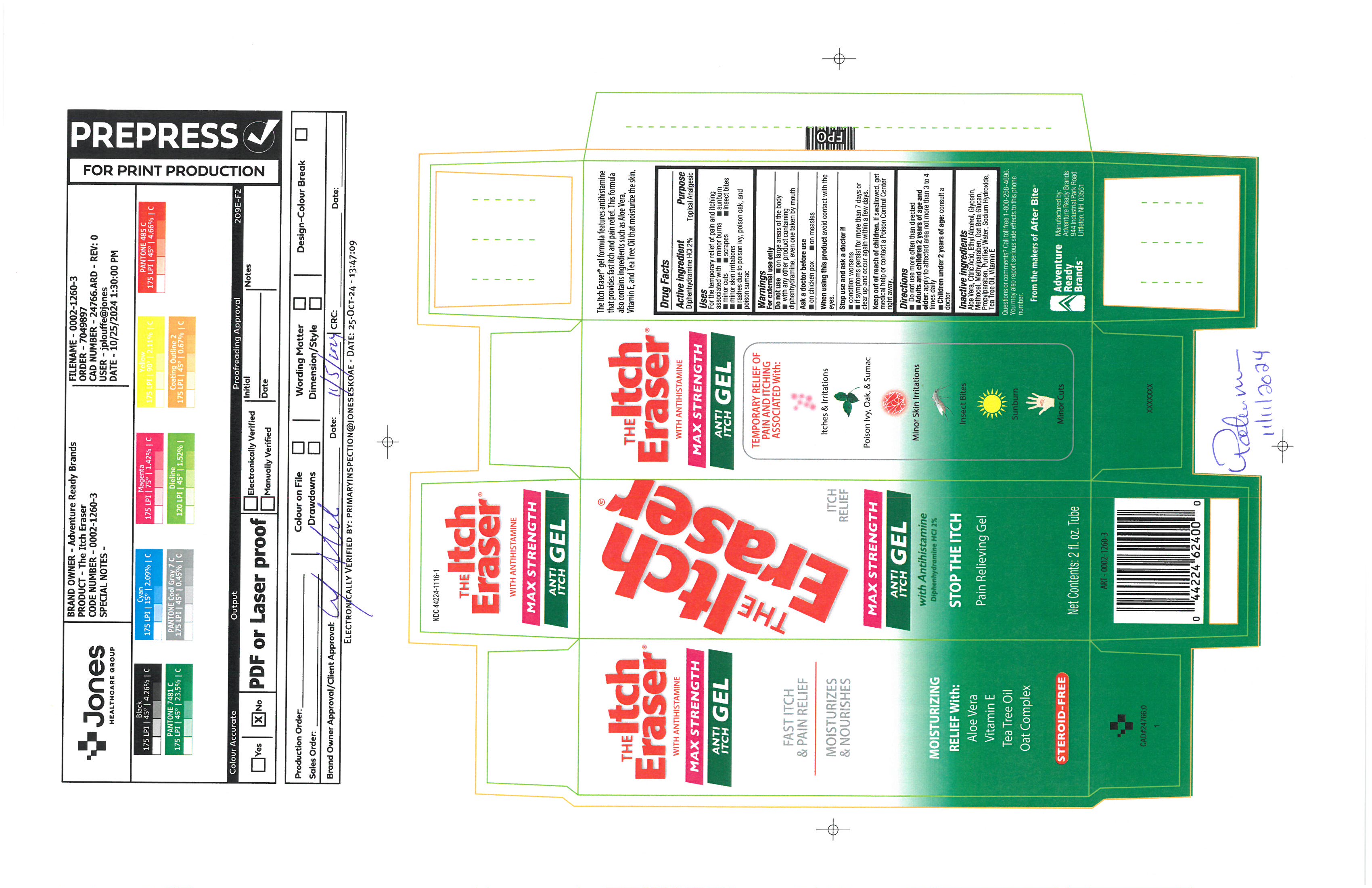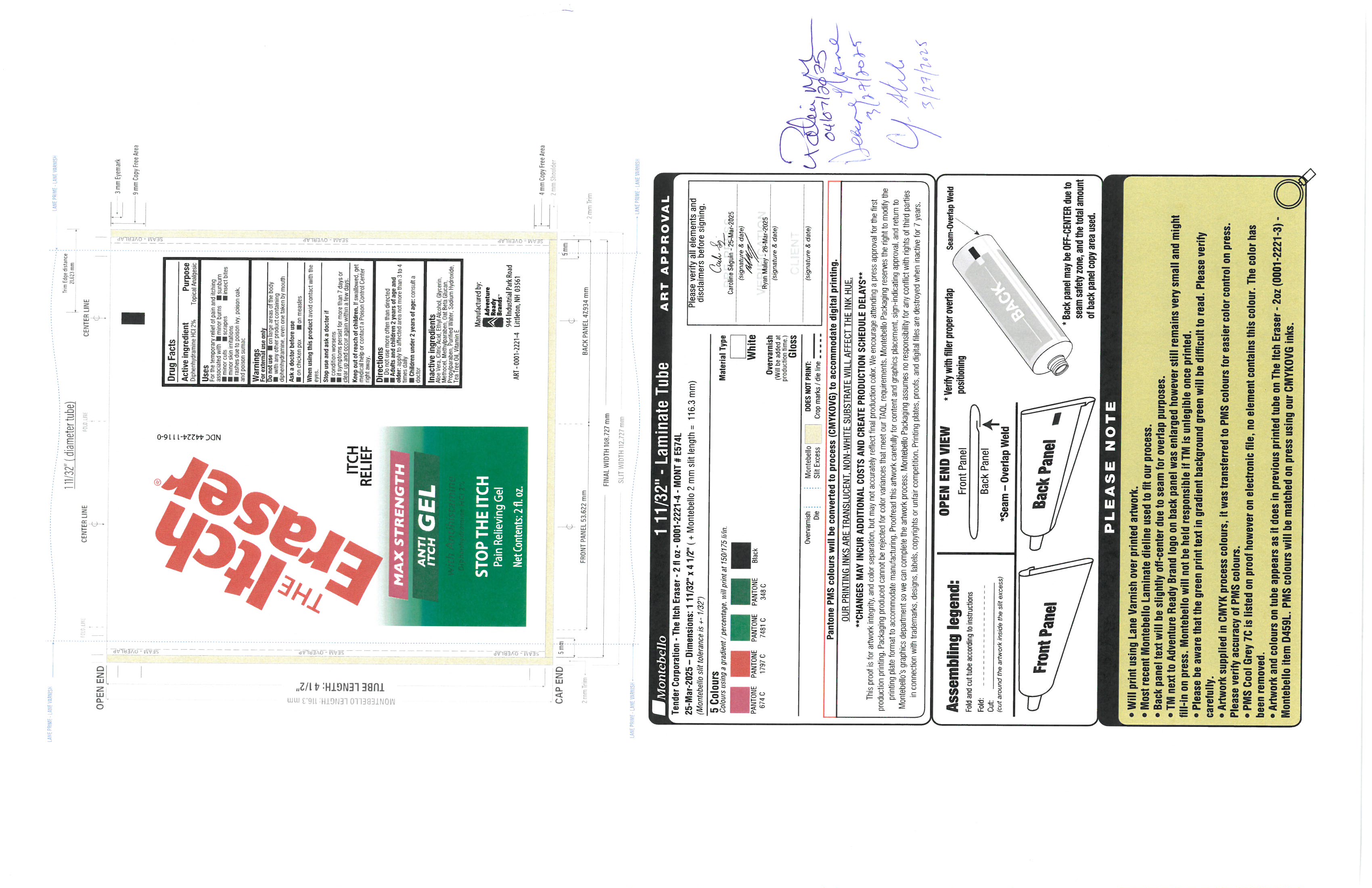 DRUG LABEL: Itch Eraser Gel
NDC: 44224-1116 | Form: GEL
Manufacturer: Tender Corporation d/b/a Adventure Ready Brands
Category: otc | Type: HUMAN OTC DRUG LABEL
Date: 20251117

ACTIVE INGREDIENTS: DIPHENHYDRAMINE 1.14 g/57 g
INACTIVE INGREDIENTS: METHYLPARABEN 0.114 g/57 g; PROPYLPARABEN 0.057 g/57 g; ALOE VERA LEAF 2.337 g/57 g; GLYCERIN 2.28 g/57 g; ALCOHOL 14.82 g/57 g; OAT 0.57 g/57 g; WATER 34.542 g/57 g; ANHYDROUS CITRIC ACID 0.125 g/57 g; .ALPHA.-TOCOPHEROL 0.171 g/57 g; SODIUM HYDROXIDE 0.0741 g/57 g; TEA TREE OIL 0.285 g/57 g; HYPROMELLOSE, UNSPECIFIED 1.14 g/57 g

Itch Eraser Gel

Active Ingredient

Diphenhydramine HCl 2%

Purpose

Topical Analgesic

Uses

For temporrary relief of pain and itching associated with minor burns, sunburn, minor cuts, scrapes, insect bites, minor skin irritations, rashes due to posion ivy, poison oak, and poison sumac

Warnings

For external use only

do not Use

on large areas of the body, with any other product containing diphenhydramine, even one taken by mouth

Ask a Doctor before use

on chicken pox, on measles

when using this product

avoid contact with eyes

Stop use and ask a doctor if

condition worsens, if symptoms persist for more than 7 days or clear up and occur again within a few days

Keep out of reach of children

if swallowed, get medical help or contact poison control center right away

Directions

Do not use more often than directed, Adults and children 2 years of age and older: apply to affected area not more than 3 to 4 times daily.

Children under 2 years of age: consult a doctor

Inactive ingredeints

aloe vera, citric acid, ethyl alcohol, glycerin, methocel, methylparaben, oat beat glucan, propylparaben, purified water, sodium hydroxide, tea tree oil, vitamin e